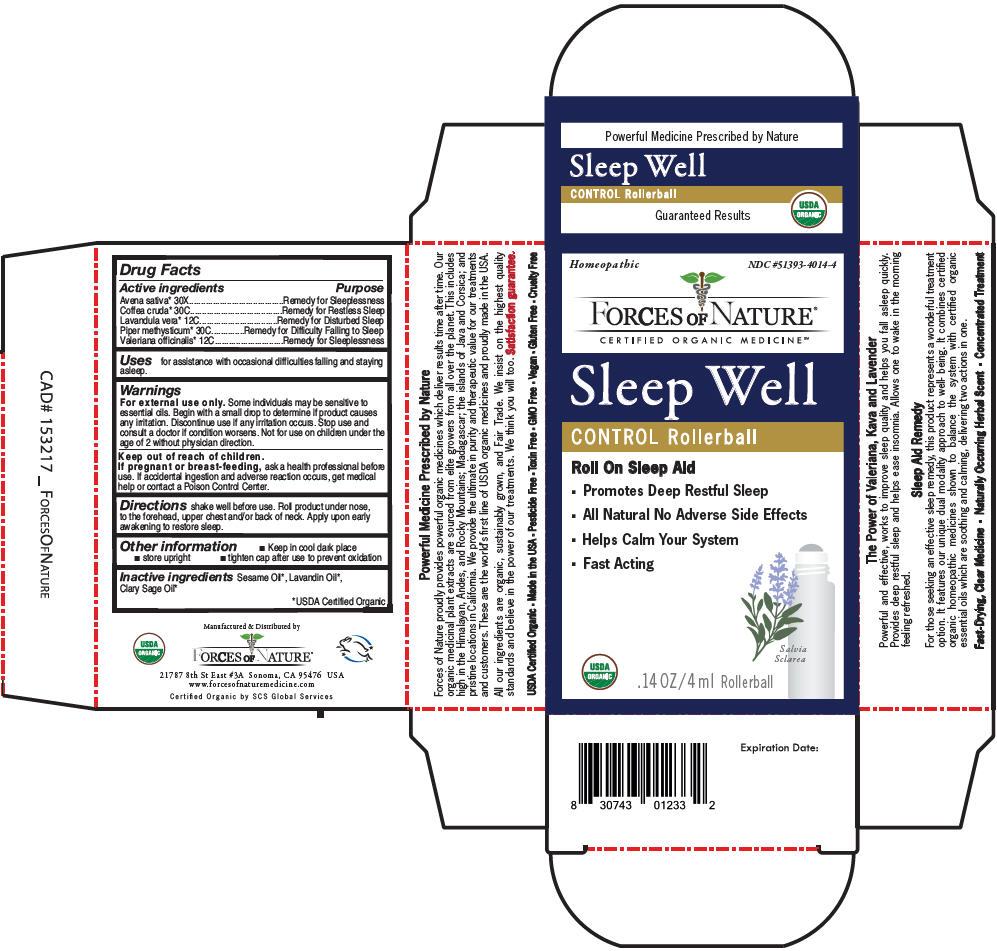 DRUG LABEL: Sleep Well 
NDC: 51393-4014 | Form: SOLUTION/ DROPS
Manufacturer: Forces of Nature
Category: homeopathic | Type: HUMAN OTC DRUG LABEL
Date: 20200428

ACTIVE INGREDIENTS: Avena Sativa Flowering Top 30 [hp_X]/100 mL; Arabica Coffee Bean 30 [hp_C]/100 mL; Lavandula Angustifolia Subsp. Angustifolia Flower 12 [hp_C]/100 mL; Macropiper Methysticum Root 30 [hp_C]/100 mL; Valerian 12 [hp_C]/100 mL
INACTIVE INGREDIENTS: Sesame Oil; Lavandin Oil; Clary Sage Oil

Sleep Well
Control

Drug Facts

ACTIVE INGREDIENT

Active ingredients | Purpose
Avena sativa [USDA Certified Organic] 30X | Remedy for Sleeplessness
Coffea cruda 30C | Remedy for Restless Sleep
Lavandula vera 12C | Remedy for Disturbed Sleep
Piper methysticum 30C | Remedy for Difficulty Falling to Sleep
Valeriana officinalis 12C | Remedy for Sleeplessness

Uses

for assistance with occasional difficulties falling and staying asleep.

Warnings

For external use only. Some individuals may be sensitive to essential oils. Begin with a small drop to determine if product causes any irritation. Discontinue use if any irritation occurs. Stop use and consult a doctor if condition worsens. Not for use on children under the age of 2 without physician direction.

Keep out of reach of children.

PREGNANCY OR BREAST FEEDING

If pregnant or breast-feeding, ask a health professional before use. If accidental ingestion and adverse reaction occurs, get medical help or contact a Poison Control Center.

Directions

shake well before use. Roll product under nose, to the forehead, upper chest and/or back of neck. Apply upon early awakening to restore sleep.

Other information

- Keep in cool dark place
- store upright
- tighten cap after use to prevent oxidation

Inactive ingredients

Sesame Oil, Lavandin Oil, Clary Sage Oil

Manufactured & Distributed by

FORCES OF NATURE®

21787 8th St East #3A Sonoma, CA 95476 USA

PRINCIPAL DISPLAY PANEL - 4 ml Bottle Carton

Homeopathic
NDC #51393-4014-4

FORCES OF NATURE®

CERTIFIED ORGANIC MEDICINE℠

Sleep Well

CONTROL Rollerball

Roll On Sleep Aid

- Promotes Deep Restful Sleep
- All Natural No Adverse Side Effects
- Helps Calm Your System
- Fast Acting

Salvia
Sclarea

USDA
ORGANIC

.14 OZ/4 ml Rollerball